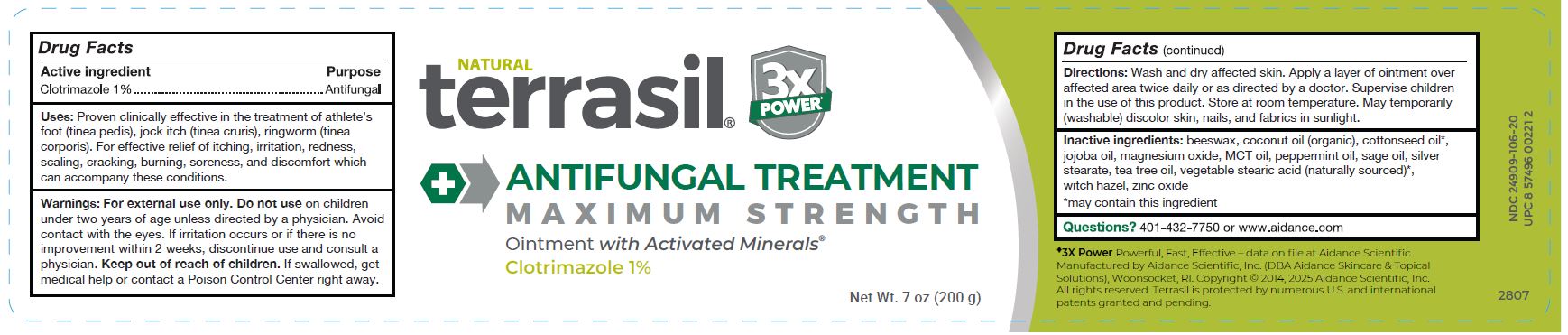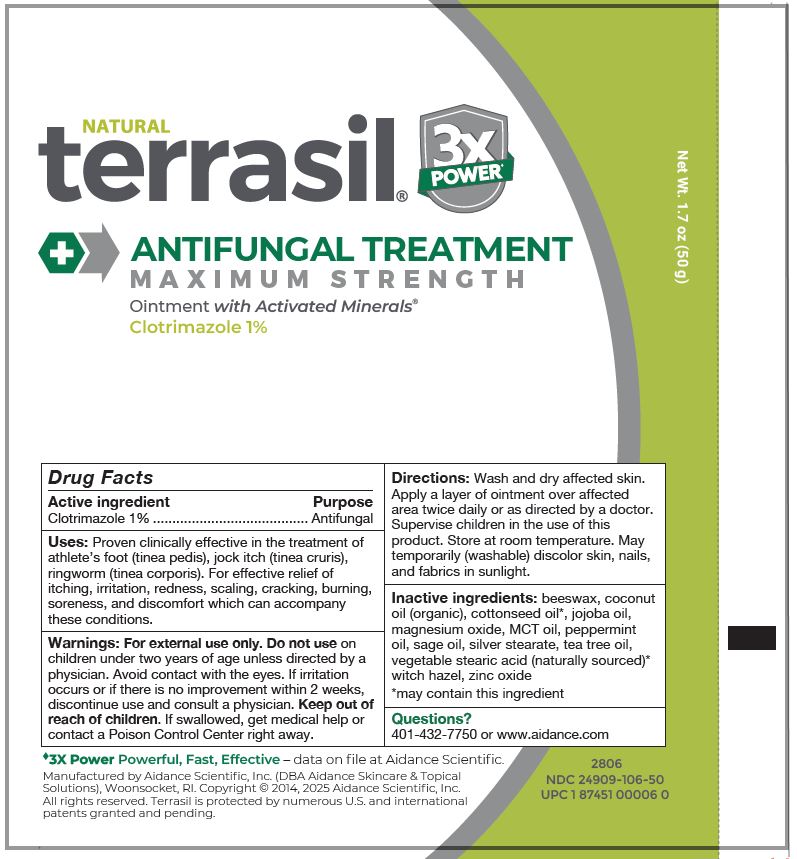 DRUG LABEL: Terrasil Anti-Fungal Treatment
NDC: 24909-106 | Form: OINTMENT
Manufacturer: Aidance Scientific, Inc., DBA Aidance Skincare & Topical Solutions
Category: otc | Type: HUMAN OTC DRUG LABEL
Date: 20250523

ACTIVE INGREDIENTS: CLOTRIMAZOLE 1 g/100 g
INACTIVE INGREDIENTS: YELLOW WAX; COCONUT OIL; COTTONSEED OIL; JOJOBA OIL; MAGNESIUM OXIDE; PALM OIL; PEPPERMINT OIL; SAGE OIL; SILVER STEARATE; TEA TREE OIL; WITCH HAZEL; ZINC OXIDE; STEARIC ACID

24909-106 terrasil Antifungal Treatment Max

Active Ingredient

Clotrimazole 1%

Purpose

Antifungal

Uses

Proven clinically effective in the treatment of athlete’s foot (tinea pedis), jock itch (tinea cruris), ringworm (tinea corporis). For effective relief of itching, irritation, redness, scaling, cracking, burning, soreness, and discomfort which can accompany these conditions.

Warnings

For external use only. Do not useon children under two years of age unless directed by a physician. Avoid contact with the eyes. If irritation occurs or if there is no improvement within 2 weeks, discontinue use and consult a physician. Keep out of reach of children. If swallowed, get medical help or contact a Poison Control Center right away.

Directions

Wash and dry affected skin. Apply a layer of ointment over affected area twice daily or as directed by a doctor. Supervise children in the use of this product.

Inactive Ingredients

beeswax, coconut oil (organic), cottonseed oil*, jojoba oil, magnesium oxide, MCT oil, peppermint oil, sage oil, silver stearate, tea tree oil, vegetable stearic acid (naturally sourced)*, witch hazel, zinc oxide

*may contain this ingredient

Other information

Store at room temperature. May temporarily (washable) discolor skin and fabrics in sunlight.